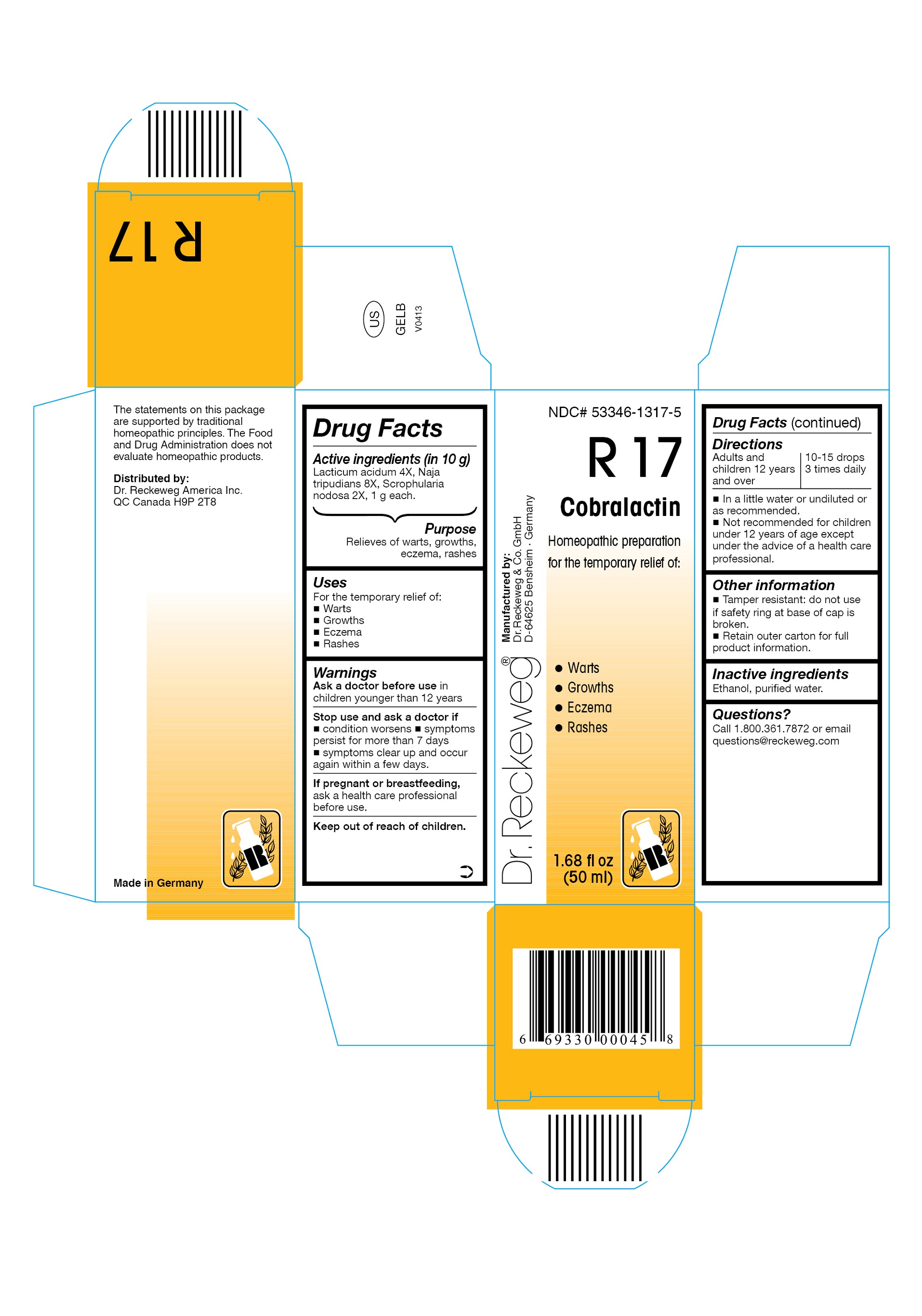 DRUG LABEL: DR. RECKEWEG R17 Cobralactin
NDC: 53346-1317 | Form: LIQUID
Manufacturer: PHARMAZEUTISCHE FABRIK DR. RECKEWEG & CO
Category: homeopathic | Type: HUMAN OTC DRUG LABEL
Date: 20130404

ACTIVE INGREDIENTS: LACTIC ACID, DL- 4 [hp_X]/50 mL; NAJA NAJA VENOM 8 [hp_X]/50 mL; SCROPHULARIA NODOSA 2 [hp_X]/50 mL
INACTIVE INGREDIENTS: ALCOHOL; WATER

DR. RECKEWEG R17 Cobralactin

Active ingredients

Lacticum acidum 4X, Naja tripudians 8X, Scrophularia nodosa 2X, 1 g each in 10 g.

Purpose

Relieves of warts, growths, eczema, rashes

Uses

For the temporary relief of:

- Warts
- Growths
- Eczem
- Rashes

Warnings

Ask a doctor before use

- in children younger than 12 years.

Stop use and ask a doctor if

- condition worsens
- symptoms persist for more than 7 days
- symptoms clear up and occur again within a few days.

PREGNANCY OR BREAST FEEDING

If pregnant or breastfeeding, ask a health care professional before use.

Keep out of reach of children.

Directions
Adults and children ≥ 12 years 10-15 drops 3 times daily in a little water or undiluted or as recommended.

Not recommended for children under 12 years of age except under the advice of a health care professional.

Other information

- Tamper resistant: do not use if safety ring at base of cap is broken.
- Retain outer carton for full product information.

Inactive ingredients
Ethanol, purified water.

Questions?
Call 1-800-361-7872 or email questions@reckeweg.com

PACKAGE LABEL

NDC# 53346-1317-5

Dr. Reckeweg R17 Cobralactin

Homeopathic preparation for the temporary relief of:

- Warts
- Growths
- Eczema
- Rashes

Manufactured by:

Dr. Reckeweg Co. GmbH

D-64625 Bensheim

Germany

1.68 fl oz
(50 ml)